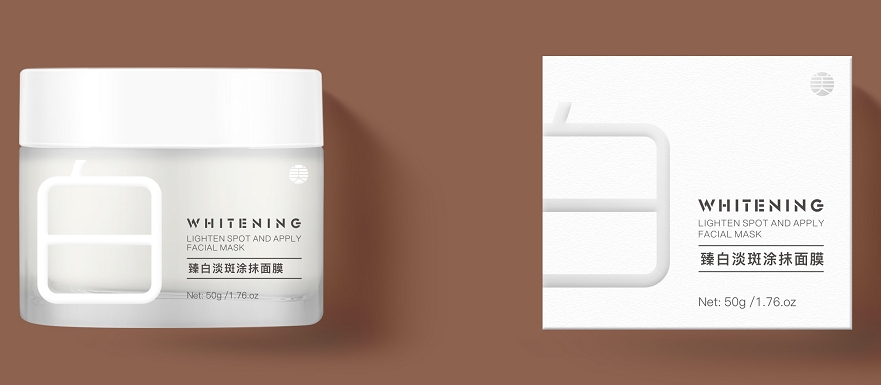 DRUG LABEL: Whitening cream
NDC: 84507-014 | Form: CREAM
Manufacturer: Guangdong Miaolian Cosmetics Co., Ltd.
Category: otc | Type: HUMAN OTC DRUG LABEL
Date: 20240819

ACTIVE INGREDIENTS: 3-O-ETHYL ASCORBIC ACID 0.4 mg/100 g
INACTIVE INGREDIENTS: WATER

DOSAGE AND ADMINISTRATION

For external use only, avoid contact with eyes when used

WARNINGS

1. Before use, perform a skin test on your arm and discontinue
use if you have allergy symptoms or skin abnormalities.
2. For external use only, avoid contact with eyes when used
3. Keep out of reach of children

INACTIVE INGREDIENT

water..

INDICATIONS AND USAGE

Before using this Day Face Cream, Kindly remove all the impurities from your face. Apply and massage for sometimes. The first result can be seen after 7 days.

Keep out of reach of children

PURPOSE

For Face Whitening and Hydrating